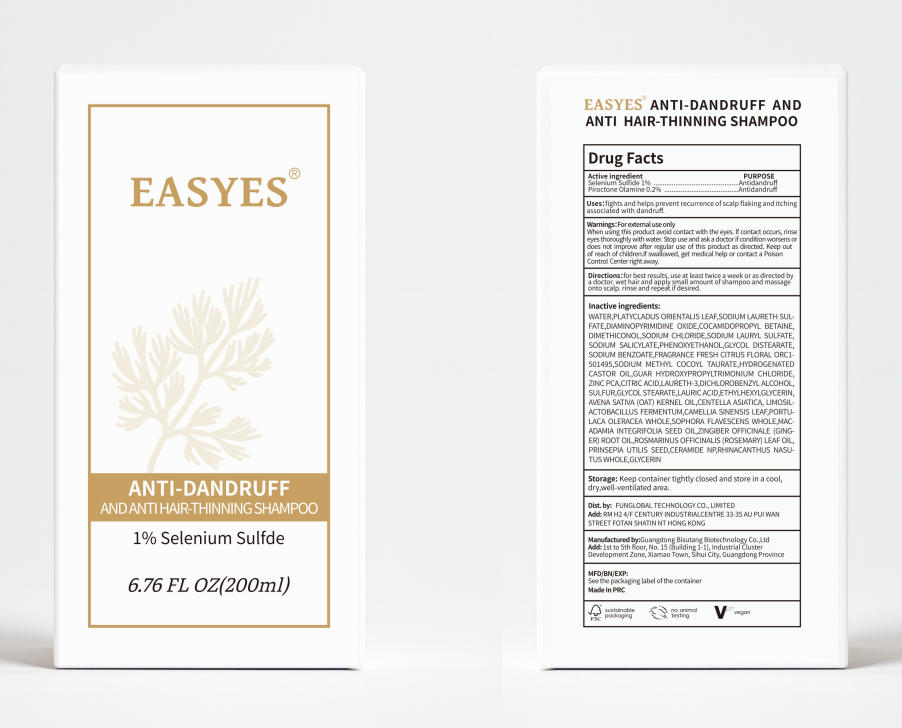 DRUG LABEL: EASYES ANTI-DANDRUFF AND ANTI HAIR-THINNING SHAM-POO
NDC: 84753-036 | Form: SHAMPOO
Manufacturer: Guangdong Bisutang Biotechnology Co., LTD
Category: otc | Type: HUMAN OTC DRUG LABEL
Date: 20250824

ACTIVE INGREDIENTS: SELENIUM SULFIDE 1 mg/100 mL
INACTIVE INGREDIENTS: SODIUM BENZOATE; PIROCTONE OLAMINE; WATER; GLYCERIN; SODIUM LAURYL SULFATE; PORTULACA OLERACEA WHOLE; SOPHORA FLAVESCENS WHOLE; CENTELLA ASIATICA; CAMELLIA SINENSIS LEAF; GLYCOL DISTEARATE; FRAGRANCE FRESH CITRUS FLORAL ORC1501495; SODIUM CHLORIDE; PRINSEPIA UTILIS SEED; COCAMIDOPROPYL BETAINE; DIMETHICONOL (14000 CST); SODIUM METHYL COCOYL TAURATE; GUAR HYDROXYPROPYLTRIMONIUM CHLORIDE; ZINC PCA; LAURIC ACID; AVENA SATIVA (OAT) KERNEL OIL; SODIUM LAURETH SULFATE; CITRIC ACID; SULFUR; GLYCOL STEARATE; ETHYLHEXYLGLYCERIN; ZINGIBER OFFICINALE (GINGER) ROOT OIL; CERAMIDE NP; RHINACANTHUS NASUTUS WHOLE; DIAMINOPYRIMIDINE OXIDE; SODIUM SALICYLATE; LIMOSILACTOBACILLUS FERMENTUM; PHENOXYETHANOL; LAURETH-3; PLATYCLADUS ORIENTALIS LEAF; MACADAMIA INTEGRIFOLIA SEED OIL; ROSMARINUS OFFICINALIS (ROSEMARY) LEAF OIL; HYDROGENATED CASTOR OIL; DICHLOROBENZYL ALCOHOL

INACTIVE INGREDIENT

WATER
SODIUM LAURETH SULFATE
COCAMIDOPROPYL BETAINE
DIMETHICONOL
SODIUM CHLORIDE
DIAMINOPYRIMIDINE OXIDE
SODIUM LAURYL SULFATE
SODIUM SALICYLATE
GLYCERIN
PHENOXYETHANOL
GLYCOL DISTEARATE
SODIUM BENZOATE
FRAGRANCE FRESH CITRUS FLORAL ORC1501495
SODIUM METHYL COCOYL TAURATE
HYDROGENATED CASTOR OIL
GUAR HYDROXYPROPYLTRIMONIUM CHLORIDE
ZINC PCA
CITRIC ACID
LAURETH-3
DICHLOROBENZYL ALCOHOL
SULFUR
GLYCOL STEARATE
LAURIC ACID
ETHYLHEXYLGLYCERIN
PLATYCLADUS ORIENTALIS LEAF
AVENA SATIVA (OAT) KERNEL OIL
CENTELLA ASIATICA
LIMOSILACTOBACILLUS FERMENTUM
CAMELLIA SINENSIS LEAF
PORTULACA OLERACEA WHOLE
SOPHORA FLAVESCENS WHOLE
MACADAMIA INTEGRIFOLIA SEED OIL
ZINGIBER OFFICINALE (GINGER) ROOT OIL
ROSMARINUS OFFICINALIS (ROSEMARY) LEAF OIL
PRINSEPIA UTILIS SEED
CERAMIDE NP
RHINACANTHUS NASUTUS WHOLE

INDICATIONS AND USAGE

Fights and helps prevent recurrence ofscalp flaking and itching associated with dandruff.

DOSAGE AND ADMINISTRATION

For best results, use at least twice a week or as directed bya doctor. wet hair and apply small amount of shampoo and massageonto scalp. rinse and repeat if desired.

KEEP OUT OF REACH OF CHILDREN

Keep outof reach of children.lf swallowed, get medical help or contact a PoisonControl Center right away.

ACTIVE INGREDIENT

Selenium Sulfide 1%
Piroctone Olamine 0.2%

PURPOSE

Helps prevent recurrence ofscalp flaking and itchingassociated with dandruff.

WARNINGS

For external use onlyWhen using this product avoid contact with the eyes. lf contact occurs, rinseeyes thoroughly with water, Stop use and ask a doctor if condition worsens ordoes not improve after regular use of this product as directed. Keep outof reach of children.lf swallowed, get medical help or contact a PoisonControl Centerright away.